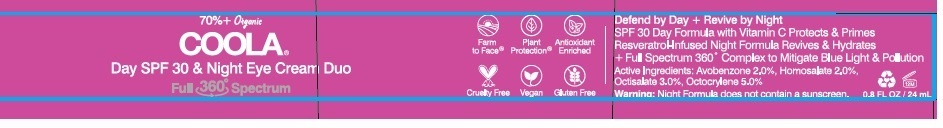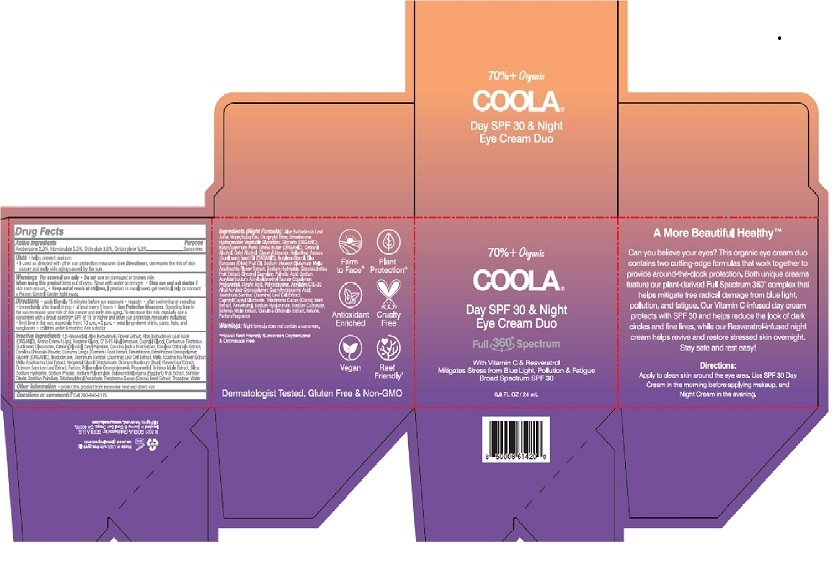 DRUG LABEL: COOLA Full Spectrum 360 Day Eye Cream SPF 30
NDC: 79753-017 | Form: CREAM
Manufacturer: COOLA LLC
Category: otc | Type: HUMAN OTC DRUG LABEL
Date: 20210203

ACTIVE INGREDIENTS: AVOBENZONE 2.0 g/100 mL; HOMOSALATE 2.0 g/100 mL; OCTISALATE 3.0 g/100 mL; OCTOCRYLENE 5.0 g/100 mL
INACTIVE INGREDIENTS: 1,2-HEXANEDIOL; ALOE VERA FLOWER; ALOE VERA LEAF; BUTYLENE GLYCOL; ALKYL (C12-15) BENZOATE; CAPRYLYL GLYCOL; CARTHAMUS TINCTORIUS (SAFFLOWER) OLEOSOMES; CETOSTEARYL ALCOHOL; CETYL PALMITATE; COCCINIA GRANDIS LEAF; CORALLINA OFFICINALIS; TURMERIC; DIMETHICONE; DIMETHICONE CROSSPOLYMER (450000 MPA.S AT 12% IN CYCLOPENTASILOXANE); GLYCERIN; ISODODECANE; JASMINUM SAMBAC FLOWER; AZADIRACHTA INDICA FLOWER; HOLY BASIL LEAF; AMMONIUM ACRYLOYLDIMETHYLTAURATE, DIMETHYLACRYLAMIDE, LAURYL METHACRYLATE AND LAURETH-4 METHACRYLATE COPOLYMER, TRIMETHYLOLPROPANE TRIACRYLATE CROSSLINKED (45000 MPA.S); PROPANEDIOL; SCHINUS MOLLE FRUITING TOP; SILICON DIOXIDE; SODIUM HYDROXIDE; PHYTATE SODIUM; SODIUM POLYACRYLATE (2500000 MW); EGGPLANT; SORBITAN MONOOLEATE; SORBITAN MONOPALMITATE; TETRAHEXYLDECYL ASCORBATE; COCOA; TROPOLONE; WATER

COOLA Full Spectrum 360 Day Eye Cream SPF 30

Drug Facts

Active Ingredients

Avobenzone 2.0%, Homosalate 2.0%, Octisalate 3.0%, Octocrylene 5.0%

Purpose .........Suncreen

INDICATIONS AND USAGE

Uses • helps prevent sunburn

- if used as directed with other sun protection measures (see Directions), decreases the risk of skin

cancer and early skin aging caused by the sun

Warnings
For external use only • Do not use on damaged or broken skin
When using this product keep out of eyes. Rinse with water to remove. • Stop use and ask doctor if
skin rash occurs • Keep out of reach of children. If product is swallowed, get medical help or contact
a Poison Control Center right away.

DOSAGE AND ADMINISTRATION

Directions • apply liberally 15 minutes before sun exposure. • reapply: ● after 80 minutes of swimming or sweating
● immediately after towel drying ● at least every 2 hours • Sun Protection Measures. Spending time in
the sun increases your risk of skin cancer and early skin aging. To decrease this risk, regularly use a
sunscreen with a broad spection SPF of 15 or higher and other sun protection measures including:
● limit time in the sun, especially from: 10 a.m. - 2 p.m. ● wear long-sleeve shirts, pants, hats, and
sunglasses ●Children under 6 months: Ask a doctor

INACTIVE INGREDIENT

Inactive Ingredients 1,2-HEXANEDIOL, Aloe Barbadensis Flower Extract, Aloe Barbadensis Leaf Juice
(ORGANIC), Amino Esters-1(JPN), Butylene Glycol, C12-15 Alkyl Benzoate, Caprylyl Glycol, Carthamus Tinctorius
(Safflower) Oleosomes, Cetearyl Alcohol , Cetyl Palmitate, Coccinia Indica Fruit Extract, Corallina Officinalis Extract,
Corallina Officinalis Powder, Curcuma Longa (Turmeric) Root Extract, Dimethicone, Dimethicone Crosspolymer,
Glycerin (ORGANIC), Isododecane, Jasminum Sambac (Jasmine) Leaf Cell Extract, Melia Azadirachta Flower Extract,
Melia Azadirachta Leaf Extract, Neopentyl Glycol Diheptanoate, Ocimum Basilicum (Basil) Flower/Leaf Extract,
Ocimum Sanctum Leaf Extract, Parfum, Polyacrylate Crosspolymer-6, Propanediol, Schinus Molle Extract, Silica,
Sodium Hydroxide, Sodium Phytate, Sodium Polyacrylate, Sodium Melongena (Eggplant) Fruit Extract, Sorbitan
Oleate, Sorbitan Palmitate, Tetrahexyldecyl Ascorbate, Theobroma Cacao (Cocoa) Seed Extract, Tropolone, Water

Other information • protect this product from excessive heat and direct sun

Questions or comments? Call 760-940-2125

COOLA Label

SPF

30

70%+ Organic

COOLA®

Day SPF 30 & Night

Eye Cream Duo

Full 360° Spectrum

With Vitamin C & Resveratrol

Stress from Blue Light, Pollution & Fatigue

Broad Spectrum SPF 30

0.8 FL OZ / 24 mL

©2021 COOLA. Distributed by: COOLA LLC, located in Sunny &

Cool San Diego, CA 92010. All Rights Reserved. www.coola.com

*Hawaii Reef Friendly Sunscreen Oxybenzone & Octinoxate Free

res